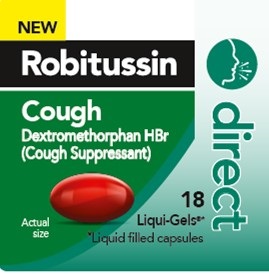 DRUG LABEL: Robitussin Direct Cough
NDC: 0031-9302 | Form: CAPSULE, LIQUID FILLED
Manufacturer: Haleon US Holdings LLC
Category: otc | Type: HUMAN OTC DRUG LABEL
Date: 20240318

ACTIVE INGREDIENTS: DEXTROMETHORPHAN HYDROBROMIDE 15 mg/1 1
INACTIVE INGREDIENTS: FD&C BLUE NO. 1; FD&C RED NO. 40; COCONUT OIL; GELATIN, UNSPECIFIED; GLYCERIN; MANNITOL; POLYETHYLENE GLYCOL, UNSPECIFIED; POVIDONE, UNSPECIFIED; PROPYL GALLATE; PROPYLENE GLYCOL; WATER; SORBITOL

Drug Facts

Active ingredient (in each liquid-filled capsule)

Dextromethorphan HBr, USP 15 mg

Purpose

Cough suppressant

Use

temporarily relieves cough due to minor throat and bronchial irritation as may occur with a cold.

Warnings

DO NOT USE

Do not useif you are now taking a prescription monoamine oxidase inhibitor (MAOI) (certain drugs for depression, psychiatric, or emotional conditions, or Parkinson's disease), or for 2 weeks after stopping the MAOI drug. If you do not know if your prescription drug contains an MAOI, ask a doctor or pharmacist before taking this product.

Ask a doctor before use if you have

- a cough that occurs with too much phlegm (mucus)
- a cough that lasts or is chronic as occurs with smoking, asthma, or emphysema

Stop use and ask a doctor ifcough lasts for more than 7 days, comes back, or is accompanied by fever, rash, or persistent headache. These could be signs of a serious condition.

PREGNANCY OR BREAST FEEDING

If pregnant or breast-feeding,ask a health professional before use.

Keep out of reach of children.In case of overdose, get medical help or contact a Poison Control Center right away.

Directions

- do not take more than 8 capsules in any 24-hour period
- this adult product is not intended for use in children under 12 years of age

adults and children 12 years and over | take 1 capsule (15 mg) every 4 hours, as required
children under 12 years | do not use

Other information

- store at 20°C-25°C (68°F -77°F)
- avoid excessive heat above 40°C (104°F)
- protect from light

Inactive ingredients

FD&C blue no. 1, FD&C red no. 40, fractionated coconut oil, gelatin, glycerin, mannitol, pharmaceutical ink, polyethylene glycol, povidone, propyl gallate, propylene glycol, purified water, sorbitol, sorbitol anhydrides

Questions or comments?

Call weekdays from 9 AM-5 PM EST at 1-800-245-1040

Additional Information

Do not use if safety seal under cap printed with “Sealed for Your Protection” is broken or missing.

Should be 18 or older to purchase

PARENTS:

Learn about teen medicine abuse

www.StopMedicineAbuse.org

Lift Here for More Drug Facts

Distributed by: GSK Consumer Healthcare, Warren, NJ 07059

visit www.robitussin.com

Trademarks owned or licensed by GSK.

©2022 GSK or licensor.

Made in India

PRINCIPAL DISPLAY PANEL

NEW

Robitussin

Cough

Dextromethorphan HBr
(Cough Suppressant)

direct

Actual size

18
Liqui-Gels®*
*Liquid filled capsules

L-0630-782-44-UPC_ORG Front Label